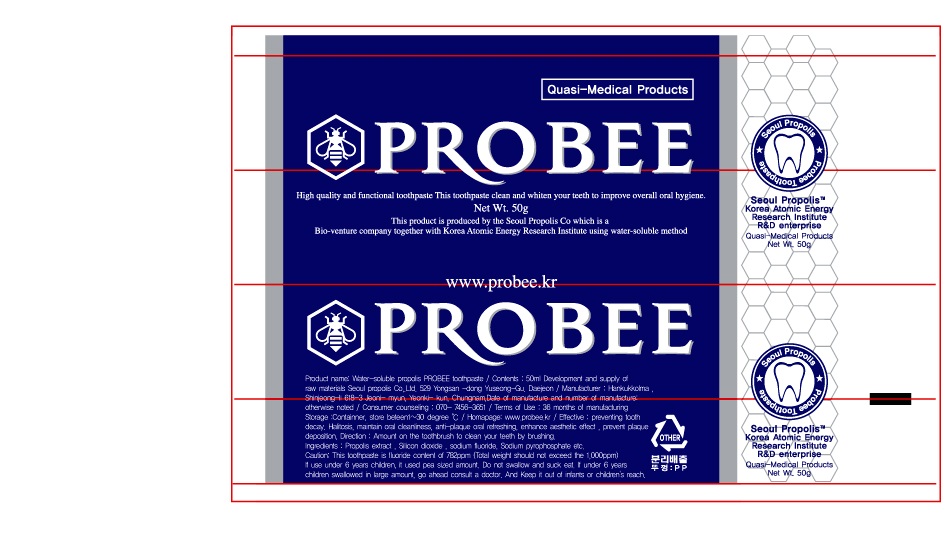 DRUG LABEL: Probee
NDC: 76254-1001 | Form: PASTE, DENTIFRICE
Manufacturer: Seoul Propolis
Category: otc | Type: HUMAN OTC DRUG LABEL
Date: 20171228

ACTIVE INGREDIENTS: PROPOLIS WAX 5 g/100 g
INACTIVE INGREDIENTS: SILICON DIOXIDE; SODIUM MONOFLUOROPHOSPHATE; SODIUM FLUORIDE; SODIUM PYROPHOSPHATE; POLYETHYLENE GLYCOL 1500; ALPHA-TOCOPHEROL ACETATE; CARBOXYMETHYLCELLULOSE SODIUM; XYLITOL; GREEN TEA LEAF; MENTHOL; PEPPERMINT; MINT; WATER

Drug Facts

ACTIVE INGREDIENT

propolis

inactive ingredient: silica dioxide, sodium monofluorophosphate, sodium fluoride, sodium pyrophosphate, polyethylene glycol 1500, tocopherol acetate, sodium carboxymethyl cellulose, xylitol, hydrate sodium saccharine, green tea extract, menthol, green tea flavor, peppermint flavor, mint flavor, purified water

PURPOSE

for dental care use

keep out of reach of the children

INDICATIONS AND USAGE

brush your teeth by putting appropriate amount of tooth paste

do not use other than oral cavity

DOSAGE AND ADMINISTRATION

Make teeth strong. Clean and refresh oral cavity. Prevent dental cavities and bad breath.
Prevent from gingivitis, paradentitis, periodontal disease and gum disease and anti plaque.